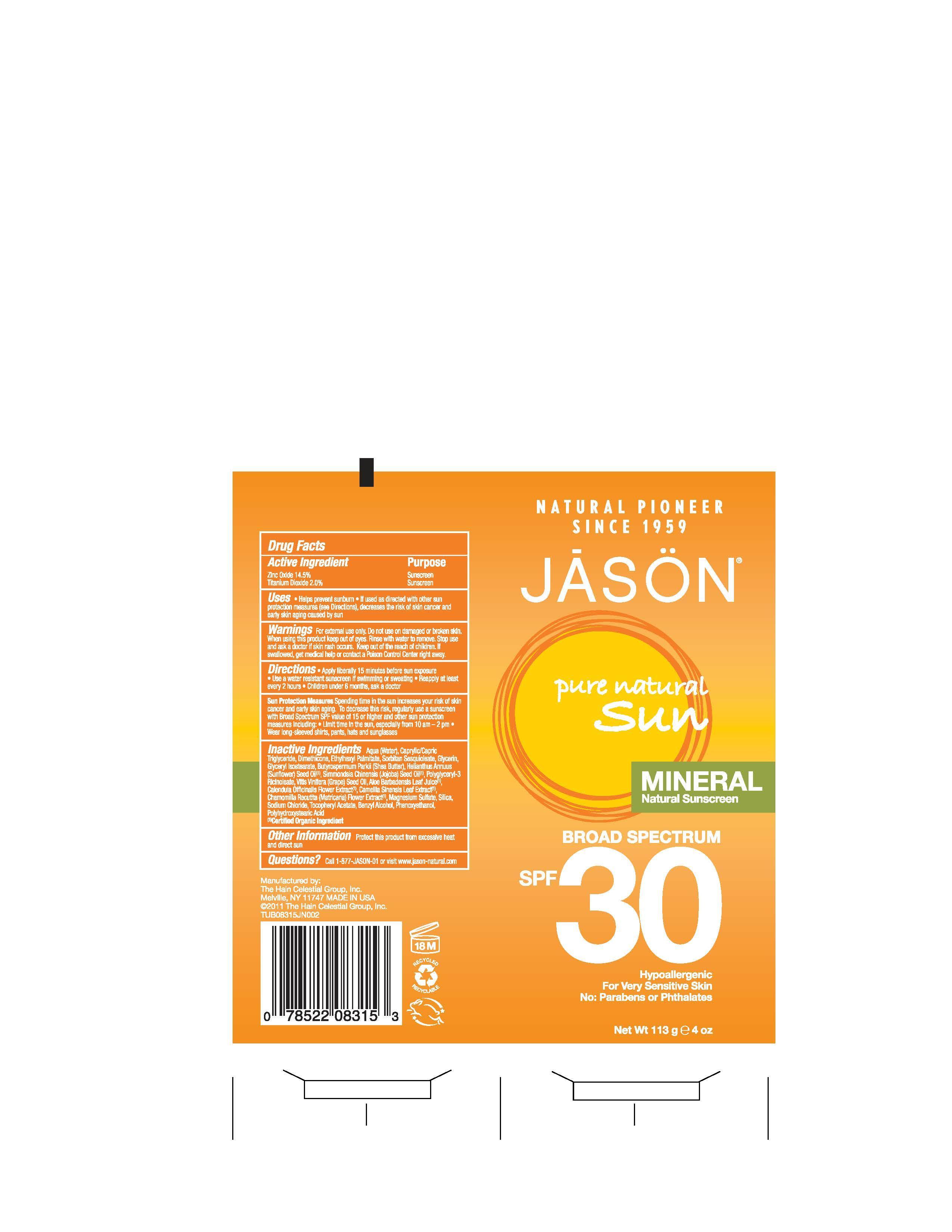 DRUG LABEL: Jason Pure Natural Sun Mineral Natural Sunscreen Broad Spectrum SPF30
                
NDC: 61995-0315 | Form: LOTION
Manufacturer: The Hain Celestial Group, Inc.
Category: otc | Type: HUMAN OTC DRUG LABEL
Date: 20120920

ACTIVE INGREDIENTS: ZINC OXIDE        14.5 g/100 g; TITANIUM DIOXIDE 2.0 g/100 g
INACTIVE INGREDIENTS: WATER; MEDIUM-CHAIN TRIGLYCERIDES; DIMETHICONE; ETHYLHEXYL PALMITATE; SORBITAN SESQUIOLEATE; GLYCERIN; GLYCERYL ISOSTEARATE; SHEA BUTTER; SUNFLOWER OIL; JOJOBA OIL; GRAPE SEED OIL; ALOE VERA LEAF; CALENDULA OFFICINALIS FLOWER; CHAMOMILE; GREEN TEA LEAF; MAGNESIUM SULFATE; SILICON DIOXIDE; SODIUM CHLORIDE; .ALPHA.-TOCOPHEROL ACETATE; BENZYL ALCOHOL; PHENOXYETHANOL; POLYHYDROXYSTEARIC ACID (2300 MW)

Drug Facts

ACTIVE INGREDIENT

Zinc Oxide 14.5%

Titanium Dioxide 2.0%

PURPOSE

Sunscreen

INDICATIONS AND USAGE

- Helps Prevent Sunburns
- If used as described with other sunscreen protection measures, decrease the risk of skin cancer and early skin aging, caused by sun.

WARNINGS

For external use only. Do not use on damaged or broken skin. When using this product keep out of eyes. Rinse with water to remove. Stop use and ask doctor if skin rash occurs.

Keep out of reach of children. If swallowed, get medical help or contact a Poison Control Center right away.

DOSAGE AND ADMINISTRATION

Apply liberally 15 minutes before sun exposure. Use a water resistant sunscreen if swimming or sweating. Reapply at least every 2 hours. Children under 6 months, ask a doctor . Skin Protection Measures: Spending time in the sun increases your risk of skin cancer and early skin aging.To decrease risk, regularly use a sunscreen with Broad Spectrum SPF value of 15 or higher and other protective measures including:

- Limit time in the sun, especially from 10am to 2pm
- Wear long-sleeved shirts, pants, hats and sunglasses.

INACTIVE INGREDIENT

Aqua (Water), Caprylic/Capric Triglycerides, Dimethicone, Ethylhexyl Palmitate, Sorbitan Sesquioleate, Glycerin, Glyceryl Isostearate, Butyrospermum Parkii (Shea Butter), Helianthus Annuus (Sunflower) Seed Oil (1), Simmondsia Chinensis (Jojoba) Seed Oil (1), Polyglyceryl-3 Ricinoleate, Vitis Vinifera (Grape) Seed) Oil,Aloe Barbadensis Leaf Juice (1), Calendula Officinalis Flower Extract (1),Chamomilla Recutita (Matricaria) Flower Extract (1), Camellia Sinensis Leaf Extract (1), Magnesium Sulfate, Silica, Sodium Chloride,Tocopheryl Acetate, Benzyl Alcohol, Phenoxyethanol, Polyhydroxystearic Acid.

(1) Certified Organic Ingredients

QUESTIONS

Questions? Call 1-877 JASON-01 or visit www.Jason-natural.com